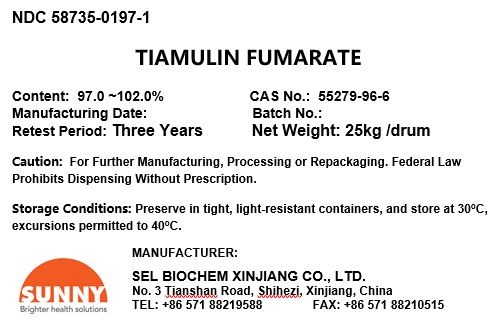 DRUG LABEL: Tiamulin Fumarate
NDC: 58735-0197 | Form: POWDER
Manufacturer: Jiangsu SEL Biochem Co., LTD.
Category: other | Type: BULK INGREDIENT - ANIMAL DRUG
Date: 20210721

ACTIVE INGREDIENTS: TIAMULIN FUMARATE 24.25 kg/25 kg

Tiamulin Fumarate

PACKAGE LABEL PRINCIPAL DISPLAY PANEL

NDC 58735-0197-1
TIAMULIN FUMARATE
Content: 97.0 ~102.0% CAS No.: 55279-96-6
Manufacturing Date: Batch No.:
Retest Period: Three Years Net Weight: 25kg /drum
Caution: For Further Manufacturing, Processing or Repackaging. Federal Law Prohibits Dispensing Without Prescription.
Storage Conditions: Preserve in tight, light-resistant containers, and store at 30oC, excursions permitted to 40oC.
MANUFACTURER:
SEL BIOCHEM XINJIANG CO., LTD.
No. 3 Tianshan Road, Shihezi, Xinjiang, China
TEL: +86 571 88219588 FAX: +86 571 88210515